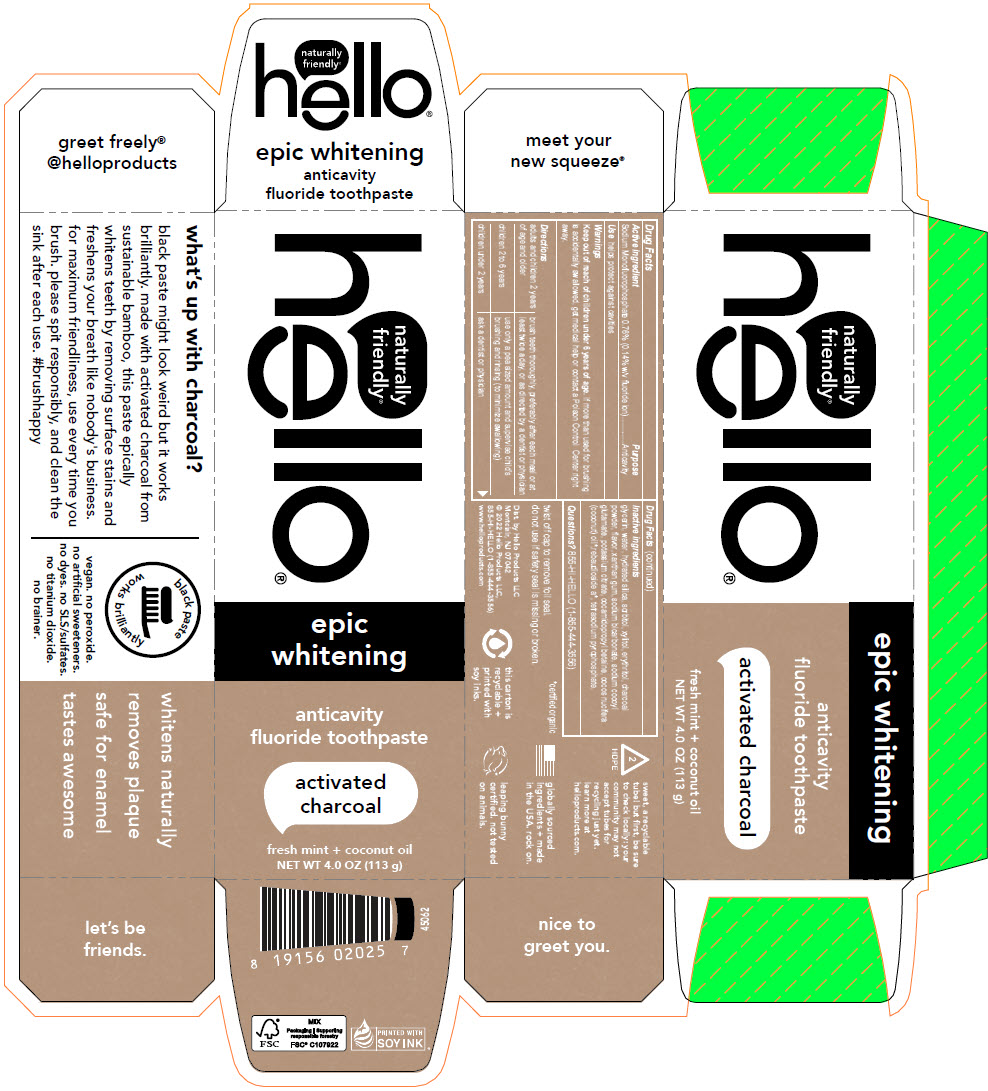 DRUG LABEL: Hello Activated Charcoal
NDC: 35000-678 | Form: PASTE, DENTIFRICE
Manufacturer: Colgate-Palmolive Company
Category: otc | Type: HUMAN OTC DRUG LABEL
Date: 20240119

ACTIVE INGREDIENTS: SODIUM MONOFLUOROPHOSPHATE 1.1 mg/1 g
INACTIVE INGREDIENTS: GLYCERIN; WATER; HYDRATED SILICA; SORBITOL; XYLITOL; ERYTHRITOL; ACTIVATED CHARCOAL; XANTHAN GUM; SODIUM BICARBONATE; SODIUM COCOYL GLUTAMATE; POTASSIUM CITRATE; COCAMIDOPROPYL BETAINE; COCONUT OIL; REBAUDIOSIDE A; SODIUM PYROPHOSPHATE

Hello® Activated Charcoal

Drug Facts

Active ingredient

Sodium Monofluorophosphate 0.76% (0.14% w/v fluoride ion)

Purpose

Anticavity

Use

helps protect against cavities

Warnings

Keep out of reach of children under 6 years of age. If more than used for brushing is accidentally swallowed, get medical help or contact a Poison Control Center right away.

Directions

adults and children 2 years of age and older | brush teeth thoroughly, preferably after each meal or at least twice a day, or as directed by a dentist or physician
children 2 to 6 years | use only a pea sized amount and supervise child's brushing and rinsing (to minimize swallowing)
children under 2 years | ask a dentist or physician

Inactive ingredients

glycerin, water, hydrated silica, sorbitol, xylitol, erythritol, charcoal powder, flavor, xanthan gum, sodium bicarbonate, sodium cocoyl glutamate, potassium citrate, cocamidopropyl betaine, cocos nucifera (coconut) oil [certified organic] ,rebaudioside a, tetrasodium pyrophosphate.

Questions?

855-HI-HELLO (1-855-444-3556)

Dist. by Hello Products LLC
Montclair, NJ 07042

PRINCIPAL DISPLAY PANEL - 113 g Tube Carton

naturally
friendly®

hello®

epic
whitening

anticavity
fluoride toothpaste

activated
charcoal

fresh mint + coconut oil

NET WT 4.0 OZ (113 g)